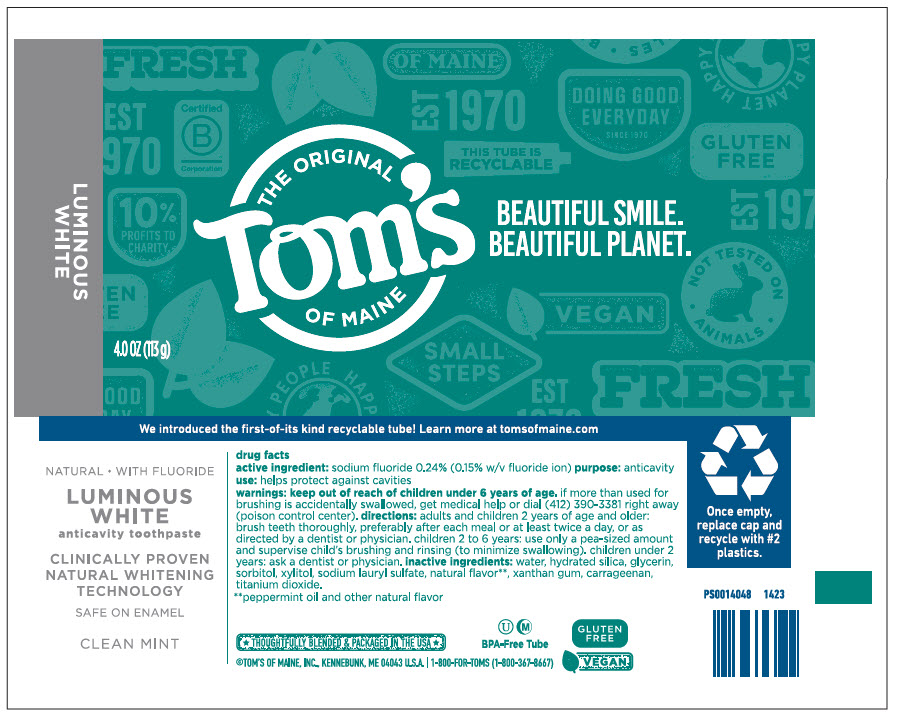 DRUG LABEL: Toms Luminous White Fluoride Clean Mint
NDC: 51009-218 | Form: PASTE, DENTIFRICE
Manufacturer: Tom's of Maine, Inc.
Category: otc | Type: HUMAN OTC DRUG LABEL
Date: 20251113

ACTIVE INGREDIENTS: SODIUM FLUORIDE 0.00243 g/1 g
INACTIVE INGREDIENTS: HYDRATED SILICA; WATER; GLYCERIN; SORBITOL; XYLITOL; SODIUM LAURYL SULFATE; PEPPERMINT OIL; XANTHAN GUM; TITANIUM DIOXIDE; CARRAGEENAN

Tom's Luminous White Fluoride Clean Mint
cavity protection / whitening

drug facts

active ingredient

sodium fluoride 0.24% (0.15% w/v fluoride ion)

purpose

anticavity

use

helps protect against cavities

warnings

keep out of reach of children under 6 years of age. if more than used for brushing is accidentally swallowed, get medical help or dial (412) 390-3381 right away (poison control center).

directions

adults and children 2 years of age and older: brush teeth thoroughly, preferably after each meal or at least twice a day, or as directed by a dentist or physician. children 2 to 6 years: use only a pea-sized amount and supervise child's brushing and rinsing (to minimize swallowing). children under 2 years: ask a dentist or physician.

inactive ingredients

water, hydrated silica, glycerin, sorbitol, xylitol, sodium lauryl sulfate, natural flavor [peppermint oil and other natural flavor] , xanthan gum, carrageenan, titanium dioxide.

PRINCIPAL DISPLAY PANEL - 113 g Tube Label

THE ORIGINAL
Tom's
OF MAINE

BEAUTIFUL SMILE.
BEAUTIFUL PLANET.

LUMINOUS
WHITE

4.0 OZ (113 g)